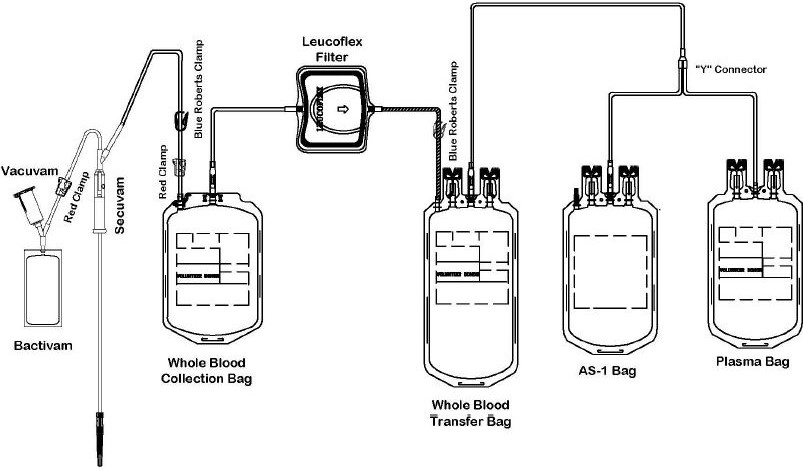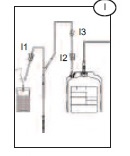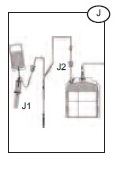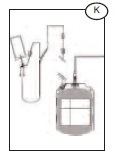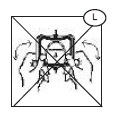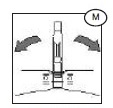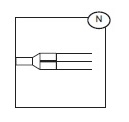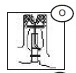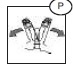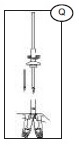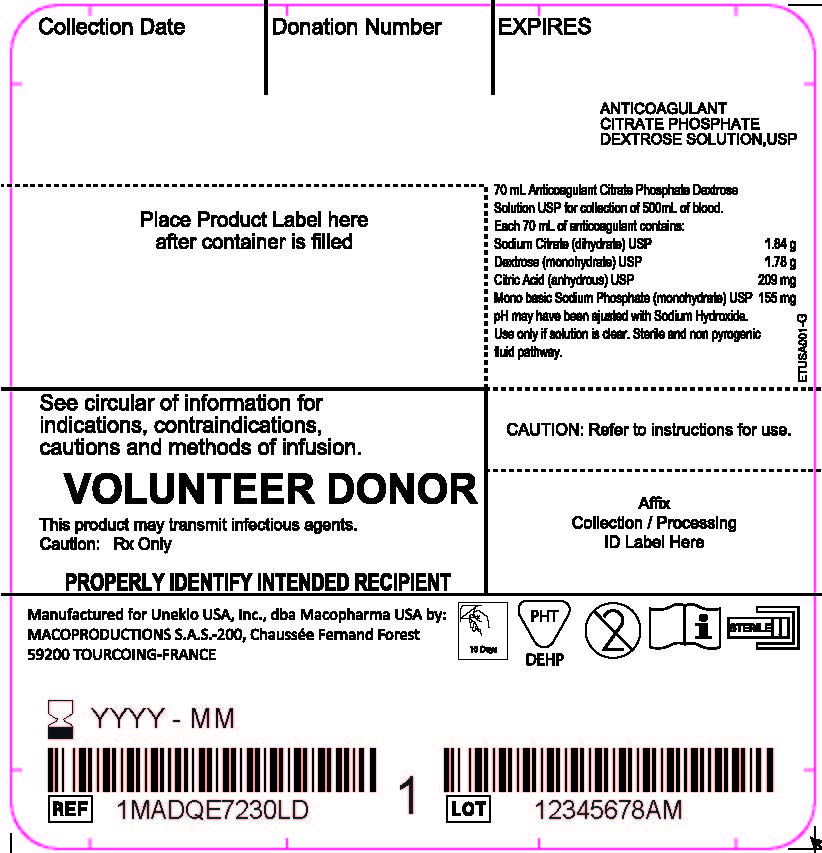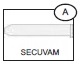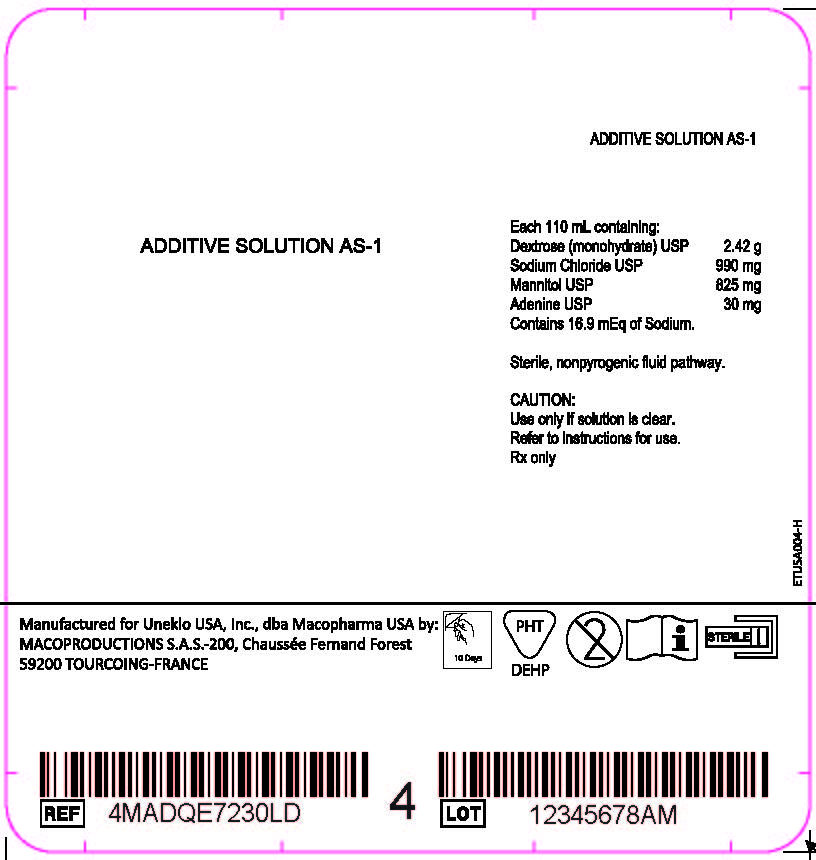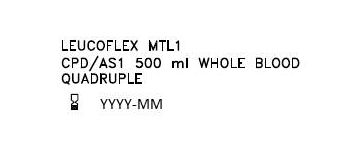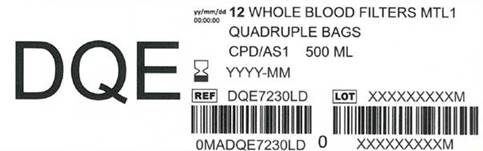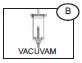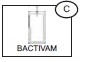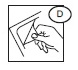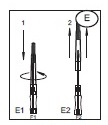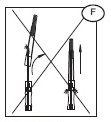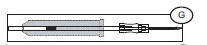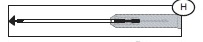 DRUG LABEL: MTL1 Leucoflex
NDC: 14498-001 | Form: KIT | Route: INTRAVENOUS
Manufacturer: Maco Productions
Category: prescription | Type: HUMAN PRESCRIPTION DRUG LABEL
Date: 20251229

ACTIVE INGREDIENTS: SODIUM CITRATE 1.84 g/70 mL; DEXTROSE MONOHYDRATE 1.78 g/70 mL; ANHYDROUS CITRIC ACID 209 mg/70 mL; SODIUM PHOSPHATE, MONOBASIC, MONOHYDRATE 155 mg/70 mL; DEXTROSE MONOHYDRATE 2.42 g/110 mL; SODIUM CHLORIDE 990 mg/110 mL; MANNITOL 825 mg/110 mL; ADENINE 30 mg/110 mL

Anticoagulant Citrate Phosphate Dextrose Solution USP (CPD)
with an integral container of Additive Solution (AS-1) preservative,
and an integral Leucoflex MTL1 Leukocyte Reduction Filter for Whole Blood

Description

The Leucoflex MTL1 product consists of a blood collection system with 70mL of CPD for the collecion of 500 +/- 50mL of blood and 110mL of AS-1 Additive Solution. They are supplied with sterile, non-pyrogenic fluid pathways. The product as supplied includes an in-line leukoreduction filter known as Leucoflex MTL1, storage containers for blood components and tubing, a sample diversion pouch (Bactivam), a vacuum tube adapter (Vacuvam), and a protective shield for the used needle (Secuvam).

Representative Product Drawing

Intended Use

The "Leucoflex MTL1 Leukocyte Reduction Filter for Whole Blood" is intended for the pre-storage leukoreduction of whole blood initiated between 4 and 7 hours after collection if whole blood is stored at ambient temperature, or between 4 and 8 hours of storage at 1 to 6 C. The collection set provides for subsequent preparation of AS-1 Red Blood Cells, Leukocytes Reduced (adenine saline added) and Plasma, Leukocytes Reduced in a closed system.

The AS-1 Red Blood Cells, Leukocytes Reduced and Plasma, Leukocytes Reduced may then be stored for the maximum allowable dating periods.

WARNING

- Avoid contact with sharp objects.
- DO NOT USE if the overwrap or blood bag system shows any signs of deterioration.
- DO NOT USE if the solutions are not clear.
- Dispose of all system components that have been contaminated with blood in a biohazard container as per your institution's SOP.
- Dispose of all sharps as per your institution's SOP.

CAUTIONS

- Do not fold or squeeze the Leucolex MTL1 filter. Inappropriate handling may adversely affect filtration.
- Check for kinks in the tubing prior to collection and filtration.
- Rx only.

The protective shield for needle Secuvam (A) and the vacuum tube adapter Vacuvam (B) features of the collection set aid in the safe collection of vacuum tube samples from the sample diversion pouch Bactivam (C) and the disposal of donor needles after blood collection by providing protection from accidental needlestick.

All or part of this medical device is made of PVC plasticized with DEHP. According to some studies, DEHP could potentially be harmful to the reproductive system of male fetuses. The prescriber is solely responsible for choosing to use this device on women who are either pregnant or breast-feeding, or on young male infants. Nevertheless, DEHP-plasticized PVC is in compliance with the European Pharmacopeia.

Risks linked to the reuse: Septic risk.

All manufacturing processes and all components in contact with the donors, the users and the blood components dedicated to the patients are not made with natural rubber latex.

COLLECTION AND SAMPLING PROCEDURE

Before Donation

1) Peel open the transparent overwrap (D) using the corner flap.

2) Support blood bag system as far as possible below donor arm, ideally on an automated blood mixer.

Note: it is recommended that the primary bag on the mixer lies with the tubing on the lower side of the mixer holding plate.

3) Apply tourniquet or pressure cuff (inflate to approximately 60 mm Hg).

4) Prepare venipuncture site as per your SOP.

5) Ensure that the donor line is not twisted or tangled.

Venipucture

1) Open the needle cap (E1) using the following procedure:

a) Twist the needle cap, thus breaking the seal.

b) Lift the cap off of the needle (E2) in a straight line taking special care not to touch the needle in the process (F). Keep hands behind the needle at all times during set use and disposal.

2) Perform the venipuncture

3) After the needle has been inserted, introduce the Secuvam onto the hub of the needle.

4) Tape the Secuvam onto the donor's arm.

Note: if the Secuvam causes discomfort to the donor or decreases the blood flow because of the angle of the needle, leave the Secuvam on the tubing, behind the needle hub (G) during collection. Secure the needle into the Secuvam at the end of the donation (H).

After Venipuncture

1) Ensure that the clamp between the Bactivam pouch and the donation line is open.

2) Ensure that the Bactivam pouch is held below the level of the venipuncture site, and is supported at all times.

3) Allow blood to run into the Bacivam pouch until the pouch fills (approximately 30ml) (I).

4) Close the red clamp (I1) on the transfer line to the Bactivam pouch, by holding the clamp in one hand and squeezing the two edges together, until it locks (a click my be heard).

Note: the red clamp cannot be opened after it has snapped shut.

5) Break the break-away cannula (I2) on the donor line by holding the cannula in one hand and the plastic Y-junction in the other and snapping the cannula both left and right to ensure a clean break. Allow the donation procedure to continue, ensuring that the blood bag is mixed immediately when blood flows into the primary bag.

Note: This step may be done prior to venipuncture if the Blue Roberts clamp (I3) on the donor line is closed prior to breaking the break-away cannula.

6) If using an automated mixer, open the mixer clamp and start the mixer at this point.

Note: it is recommended that the primary bag on the mixer lies with the tubing on the lower side of the mixer holding plate.

7) After approximately 50 ml of blood enters the primary bag, mix thoroughly (when possible).

Note: Collect the quantity of blood stated on the blood bag label.

Sampling Procedure

Note: this is done during the donation. Avoid air in the collection of sample tubes from the diversion pouch to ensure adequate sample volume and avoid hemolysis.

1) Hold the Bactivam pouch with the Vacuvam below it (J), to ensure good blood flow from the pouch to the sampling device, and no introduction of air into the sampling tubes.

2) Remove the cap of the Vacuvam sampling device, and retain for later use (when possible).

3) Introduce a vacuum sampling tube by holding the barrel of the Vacuvam and directing the sample tube cap directly onto the needle inside the device (J1).

4) Blood is drawn automatically into the sampling tube, stopping at the appropriate volume.

5) When the sample tube stops filling, withdraw the tube, ensuring that the tube is pulled out of the barrel in a straight line.

6) Repeat the sampling procedure steps (3 to 5) with all remaining sampling tubes.

7) When all samples have been taken, replace the Vacuvam cap to prevent accidental access to the interior needle (when possible).

8) Mix the blood in the primary bag regularly (approximately every 100 ml or every minute).

After Donation

1) Once the required volume of blood has been collected, close the red clamp on the donor line (J2), at least 12 inches above the primary bag.

Note: if necessary, place a Hemostat on the collection line just below the Secuvam.

2) Release the pressure cuff or tourniquet, and immediately mix the whole blood in the primary bag.

Note: if the needle was taped to the arm, and not the Secuvam, remove the tape from the needle before pulling the needle into the Secuvam (disregard step 3).

3) Remove the tape holding the Secuvam in place.

4) Remove the needle by gently pulling the needle into the barrel of the Secuvam while supporting the Secuvam with one hand (a click may be heard).

Note: if necessary, step 4 may be done before step 3.

5) Remove and discard the cap (if relevant) from the barrel of the Vacuvam, into an appropriate container.

6) Insert the Secuvam needle protector into the barrel of the Vacuvam sampling device.

7) After removing the blood from the mixer/trip scale, mix the blood unit thoroughly.

8) If the donor line is to be used for quality control, strip the line as per procedure (at least 3 times), heat-seal (place clips) and cut (between the clips), leaving sufficient line for testing purposes.

Note: if it is necessary to strip the donor line, it is recommended to strip within 4 minutes of the end of the donation, in order to avoid introducing clots into the blood bag.

9) Ideally, heat-seal the donor line as close as possible to the pack (~1 inch). Alternatively, place clips close to the blood pack and cut between the clips. Mix thoroughly during and immediately after the procedure.

Note: this is an in-line filter system; there is no need to keep the donor line for cross-matching segments.

10) Remove and discard the donor line (K) with the two red clamps, Bactivam, Vacuvam and Secuvam as per SOP.

Note: the completely protected needle after securing the Secuvam inside the rigid Vacuvam sleeve can be disposed of in general biowaste vs. a sharps container

COMPONENT PREPARATION GENERAL

1 to 6 C Filtration: Ensure that the whole blood to be filtered at cold temperature has reached 1 to 6 C and has been stored between 4 and 8 hours at 1 to 6 C. The height of the unit for filtration should be 72 to 76 inches.

Ambient (20 to 24 C) Filtration: Whole blood filtration may be initiated at room temperature between 4 and 7 hours after collection. Filtrations performed at ambient temperatures should be completed within eight hours of collection. The height of the unit for filtration should be 55 to 60 inches.

CAUTION:

· Do not fold or manhandle the filters (L).

· Do not apply pressure, either mechanical or human, to increase the flow rate of the filter.

· Units with decreased or extended filtration times may not be adequately leukoreduced, and should be evaluated for residual leukocytes and red blood cell recovery before release. Consult training materials for more information on expected length of filtration times and the applicable hold periods in clinical study data.

· Failure to achieve and maintain a closed system throughout processing results in a product that must be stored at 1 to 6 C and transfused within 24 hours.

· Fresh Frozen Plasma should be prepared between 4 and 8 hours of the whole blood donation.

· Fresh Frozen Plasma should be stored at minus 18 C or colder.

· The AS-1 additive solution must be added to the red blood cells without delay after the separation of the plasma. Whole blood in CPD alone may be stored at 1 to 6 C for up to 21 days.

· The filter has been designed and validated to meet the criteria of a leukoreduction filter for whole blood. The filter's performance must be validated using your facility's standard operating procedure (SOP) on component preparation and handling. Any filtration that fails to meet the filtration specifications established by the facility's validation should be evaluated for residual leukocytes and red blood cell (RBC) recovery after filtration.

Note that unusual attributes such as sickle cell trait, cold agglutinins, blood clotting and gel formation, and poor mixing during collection and processing of components can contribute to the failure of a filtration to meet filtration specifications. Faiure to adequately re-suspend RBC by mixing the whole blood unit thoroughly prior to filtration can result in blocked filters.

WHOLE BLOOD LEUKOREDUCTION

1) Mix the blood well.

2) Suspend the blood bag at a height of 55 to 60 inches if filtering at room temperature (20 to 24 C) or 72 to 76 inches if filtering at cold temperature (1 to 6 C).

3) Break the break-away cannula (M) on the blood bag leading to the Leucoflex MTL1 filter, by bending the cannula with a side-to-side motion.

4) Allow the blood to flow by gravity through the Leucoflex MTL1 filter into the transfer bag.

Note: Determine the status of the filtation as follows: If there is no blood flowing from below the filter, the filter is flat and the filter media is visible on the inlet side, filtration is complete.

5) Ensure there is a temporary clamp between the Leucoflex MTL1 filter and the leukoreduced blood.

6) If required, purge the air from the leukoreduced blood back into the flexible Leucoflex MTL1 filter (the filter will expand), filling the segment tubing with blood.

7) Close the temporary clamp before separating the blood and attached satellites.

8) Heat seal the segment tubing just below the Leucoflex MTL1 filter, and all along the segment tubing between the printed numbers.

Note: Do not strip the tubing below the leukocyte reduction filter. Such stripping may pull leukocytes through the filter.

9) Heat seal and discard the empty collection bag, Leucoflex MTL1 filter, temporary clamp and tubing as per SOP.

Note: Ensure that the temporary clamp is not left on the segment tubing.

10) Centrifuge the blood, satellite bag, and additive solution bag together under conditions designed to produce a separation of plasma and red blood cells.

11) Place the centrifuged blood carefully into a plasma extractor, and gently release the pressure plate.

12) Break the break-away cannula on the blood bag by bending the cannula with a side-to-side motion.

13) Express Plasma into the empty transfer bag. If Cryoprecipitate AHF (Anti- Hemophilic Factor) will be manufactured from this Plasma, put a temporary clamp between the "Y" connector (N) and the plasma bag; otherwise, add a permanent clamp.

14) Break the break-away cannula on the additive solution bag by bending the cannula with a side-to-side motion.

15) Suspend the additive solution (AS-1) bag above the RBC bag so that the additive solution drains completely into the RBC without delay.

Note: The additive solution must be mixed thoroughly with the AS-1 Red Blood Cells, Leukocytes Reduced.

16) Heat seal and disconnect the Plasma, Leukocytes Reduced (and any attached transfer bags) as per SOP. Quality control testing should be performed monthly to demonstrate that the WBC content of the plasma is <5 x 10^6 per container if the Plasma or Cryoprecipitated AHF will be labeled as Leukocytes Reduced.

17) Store the AS-1 Red Blood Cells, Leukocytes Reduced at 1-6 C for up to 42 days.

18) Should Cryoprecipitated AHF be manufactured, process the plasma bag and attached empty transfer bag as per SOP.

Clinical Studies Holding Time, Residual WBC and Percent RBC Recovery

WARNING: If unit is spiked for any reason, storage is limited to 24 hours at 1 to 6 C before transfusion.

Filtration; Temperature | n | Holding Time (Hrs); Mean (Range) | Residual WBC; (x 10^6/ unit); Mean +/-SD | Percentage; RBC Recovery; Mean +/-SD
20 to 24 C | 61 | 5.1 (4.1 - 6.7) | 0.417 +/-0.533 | 91.1 +/-3.0
1 to 6 C | 30 | 5.1 (4.6 - 6.1) | 0.197 +/-0.131 | 89.9 +/-1.9

NOTE: If either face of the filter remains white, the Whole Blood Unit has not been leucoreduced and must be discarded.

HANDLING OF PORT PROTECTORS

1) Using both hands tear the port protector as indicated. (O)

2) Hold down the port protector pieces with one hand. (P)

3) Using the free hand, take the spike and engage into the port. (Q)

4) Twist the spike to secure fully in port. (Q)

Labels: Bag 1 Anticoagulant Citrate Phosphate Dextrose Solution USP; Bag 4 Additive Solution AS-1; Overwrap; Carton

Anticoagulant Citrate Phosphate Dextrose Solution, USP - Bag 1 Label

Additive Solution AS-1 - Bag 4 Label

OVERWRAP LABEL

CARTON LABEL